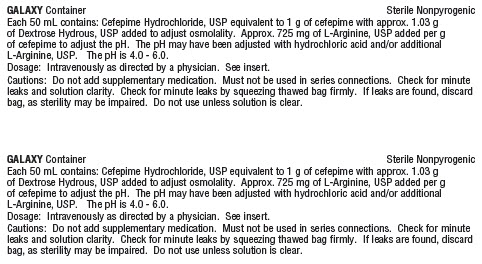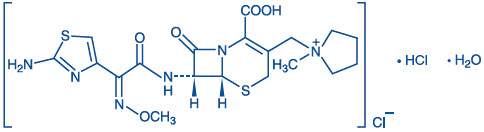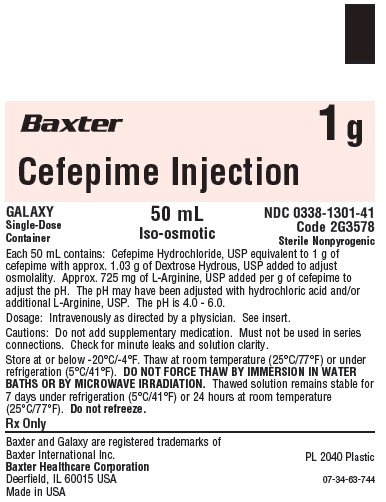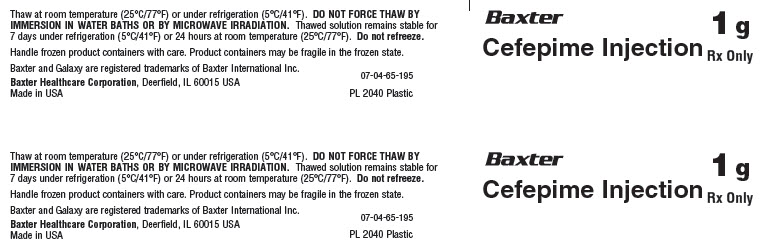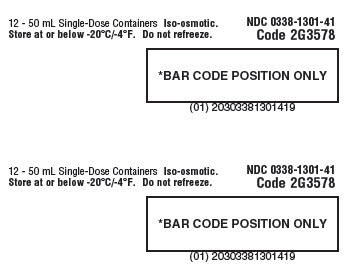 DRUG LABEL: Cefepime
NDC: 0338-1301 | Form: INJECTION, SOLUTION
Manufacturer: Baxter Healthcare Company
Category: prescription | Type: HUMAN PRESCRIPTION DRUG LABEL
Date: 20251212

ACTIVE INGREDIENTS: CEFEPIME HYDROCHLORIDE 1 g/50 mL
INACTIVE INGREDIENTS: ANHYDROUS DEXTROSE 1.03 g/50 mL; ARGININE 725 mg/50 mL; HYDROCHLORIC ACID; WATER

HIGHLIGHTS OF PRESCRIBING INFORMATION

These highlights do not include all the information needed to use CEFEPIME Injection safely and effectively. See full prescribing information for CEFEPIME Injection.
CEFEPIME injection, for intravenous use
Initial U.S. Approval: 1996

RECENT MAJOR CHANGES

Warnings and Precautions, Hypersensitivity Reactions (5.1) 12/2025

1 INDICATIONS AND USAGE

Cefepime Injection is a cephalosporin antibacterial indicated in the treatment of the following infections caused by susceptible isolates of the designated microorganisms: pneumonia (1.1); empiric therapy for febrile neutropenic patients (1.2); uncomplicated and complicated urinary tract infections (1.3); uncomplicated skin and skin structure infections (1.4); and complicated intra-abdominal infections (used in combination with metronidazole) (1.5).

To reduce the development of drug-resistant bacteria and maintain the effectiveness of Cefepime Injection and other antibacterial drugs, Cefepime Injection should be used only to treat or prevent infections that are proven or strongly suspected to be caused by bacteria. (1.6)

2 DOSAGE AND ADMINISTRATION

Recommended Dosage in Adults With Creatinine Clearance (CrCL)
Greater Than 60 mL/min (2.1)
Site and Type of Infection (Adults) | Dose (IV) | Frequency | Duration (Days)
Moderate to Severe Pneumonia [For Pseudomonas aeruginosa, use 2 g IV every 8 hours (2.1)] | 1-2 g | Every 8-12 hours | 10
Empiric therapy for febrile neutropenic patients | 2 g | Every 8 hours | 7 [Or until resolution of neutropenia (2.1)]
Mild to Moderate Uncomplicated or Complicated Urinary Tract Infections | 0.5-1 g | Every 12 hours | 7-10
Severe Uncomplicated or Complicated Urinary Tract Infections | 2 g | Every 12 hours | 10
Moderate to Severe Uncomplicated Skin and Skin Structure Infections | 2 g | Every 12 hours | 10
Complicated Intra-abdominal Infections (used in combination with metronidazole) | 2 g | Every 8-12 hours | 7-10

- Pediatric Patients (2 months to 16 years) – Recommended dosage in pediatric with CrCL greater than 60 mL/min. (2.2)
- The usual recommended dosage in pediatric patients is 50 mg per kg per dose administered every 12 hours (every 8 hours for febrile neutropenia). (2.2)
- Cefepime Injection in Galaxy Container should be used only in pediatric patients who require the entire 1 gram or 2 gram dose and not any fraction thereof. (2.2)
- Patients with Renal Impairment: Adjust dose in patients with CrCL less than or equal to 60 mL/min. (2.3)
- Administer intravenously over approximately 30 minutes. (2.1)
- Do not force thaw frozen container by immersion in water baths or by microwave irradiation. (2.4)

3 DOSAGE FORMS AND STRENGTHS

- Cefepime Injection: 1 g in 50 mL and 2 g in 100 mL single-dose Galaxy Container. (3)

4 CONTRAINDICATIONS

- Prior immediate hypersensitivity reactions to cefepime or the cephalosporin class of antibacterial drugs, penicillins, and other beta-lactam antibacterial drugs. (4)

5 WARNINGS AND PRECAUTIONS

- Cross-hypersensitivity among beta-lactam antibacterial drugs may occur in up to 10% of patients with a history of penicillin allergy. If an allergic reaction to Cefepime Injection occurs, discontinue the drug. (5.1)
- Neurotoxicity: May occur especially in patients with renal impairment administered unadjusted doses. If neurotoxicity associated with Cefepime Injection therapy occurs, discontinue the drug. (5.2)
- Clostridioides difficile Associated Diarrhea (CDAD): Evaluate if diarrhea occurs. (5.3)

6 ADVERSE REACTIONS

- The most common adverse reactions (incidence ≥ 1 %) were local reactions positive Coombs’ test, decreased phosphorous, increased ALT and AST, increased PT and PTT and rash. (6.1)
- At the highest dose (2 g every 8 hours), incidence of adverse reactions was ≥1% for rash, diarrhea, nausea, vomiting, pruritis, fever, and headache. (6.1)
To report SUSPECTED ADVERSE REACTIONS, contact Baxter at 1-866-888-2472 or FDA at 1-800-FDA-1088 or www.fda.gov/medwatch.

7 DRUG INTERACTIONS

- Aminoglycosides -- increased potential of nephrotoxicity and ototoxicity. (7.2)
- Diuretics -- nephrotoxicity has been reported following concomitant administration of other cephalosporins with potent diuretics such as furosemide. (7.3)

8 USE IN SPECIFIC POPULATIONS

- Geriatric Use – Serious adverse reactions have occurred in geriatric patients with renal impairment given unadjusted doses of cefepime. (8.5)

FULL PRESCRIBING INFORMATION

1 INDICATIONS AND USAGE

1.1 Pneumonia

Cefepime Injection is indicated for pneumonia (moderate to severe) caused by Streptococcus pneumoniae, including cases associated with concurrent bacteremia, Pseudomonas aeruginosa, Klebsiella pneumoniae, or Enterobacter species.

1.2 Empiric Therapy for Febrile Neutropenic Patients

Cefepime Injection as monotherapy is indicated for empiric treatment of febrile neutropenic patients. In patients at high risk for severe infection (including patients with a history of recent bone marrow transplantation, with hypotension at presentation, with an underlying hematologic malignancy, or with severe or prolonged neutropenia), antimicrobial monotherapy may not be appropriate. Insufficient data exist to support the efficacy of cefepime monotherapy in such patients [see Clinical Studies (14)].

1.3 Uncomplicated and Complicated Urinary Tract Infections (including pyelonephritis)

Cefepime Injection is indicated for uncomplicated and complicated urinary tract infections (including pyelonephritis) caused by Escherichia coli or Klebsiella pneumoniae, when the infection is severe, or caused by Escherichia coli, Klebsiella pneumoniae, or Proteus mirabilis, when the infection is mild to moderate, including cases associated with concurrent bacteremia with these microorganisms.

1.4 Uncomplicated Skin and Skin Structure Infections

Cefepime Injection is indicated for uncomplicated skin and skin structure infections caused by Staphylococcus aureus (methicillin-susceptible isolates only) or Streptococcus pyogenes.

1.5 Complicated Intra-abdominal Infections

Cefepime Injection is indicated for complicated intra-abdominal infections (used in combination with metronidazole) caused by Escherichia coli, viridans group streptococci, Pseudomonas aeruginosa, Klebsiella pneumoniae, Enterobacter species, or Bacteroides fragilis [see Clinical Studies (14)].

1.6 Usage

To reduce the development of drug-resistant bacteria and maintain the effectiveness of Cefepime Injection and other antibacterial drugs, Cefepime Injection should be used only to treat or prevent infections that are proven or strongly suspected to be caused by susceptible bacteria. When culture and susceptibility information are available, they should be considered in selecting or modifying antibacterial therapy. In the absence of such data, local epidemiology and susceptibility patterns may contribute to the empiric selection of therapy.

2 DOSAGE AND ADMINISTRATION

2.1 Dosage for Adults

The recommended adult dosages and routes of administration are outlined in Table 1 below for patients with creatinine clearance greater than 60 mL/min. Administer Cefepime Injection intravenously over approximately 30 minutes.

Table 1: Recommended Dosage Schedule for Cefepime Injection in Adult Patients with Creatinine Clearance (CrCL) Greater Than 60 mL/min
Site and Type of Infection | Dose | Frequency | Duration (days)
Adults
Moderate to Severe Pneumonia due to S. pneumoniae, P. aeruginosa [For Pseudomonas aeruginosa, use 2 g IV every 8 hours] , K. pneumoniae, or Enterobacter species | 1-2 g IV | Every 8-12 hours | 10
Empiric therapy for febrile neutropenic patients [see Indications and Usage (1) and Clinical Studies (14)] | 2 g IV | Every 8 hours | 7 [or until resolution of neutropenia. In patients whose fever resolves but who remain neutropenic for more than 7 days, the need for continued antimicrobial therapy should be re-evaluated frequently.]
Mild to Moderate Uncomplicated or Complicated Urinary Tract Infections, including pyelonephritis, due to E. coli, K. pneumoniae, or P. mirabilis | 0.5-1 g IV | Every 12 hours | 7-10
Severe Uncomplicated or Complicated Urinary Tract Infections, including pyelonephritis, due to E. coli or K. pneumoniae | 2 g IV | Every 12 hours | 10
Moderate to Severe Uncomplicated Skin and Skin Structure Infections due to S. aureus or S. pyogenes | 2 g IV | Every 12 hours | 10
Complicated Intra-abdominal Infections (used in combination with metronidazole) caused by E. coli, viridans group streptococci, P. aeruginosa, K. pneumoniae, Enterobacter species, or B. fragilis. [see Clinical Studies (14)] | 2 g IV | Every 8-12 hours | 7-10

2.2 Pediatric Patients (2 months up to 16 years)

The maximum dose for pediatric patients should not exceed the recommended adult dose. The usual recommended dosage in pediatric patients up to 40 kg in weight for durations as given above for adults is:

- 50 mg per kg per dose, administered every 12 hours for uncomplicated and complicated urinary tract infections (including pyelonephritis), uncomplicated skin and skin structure infections, and pneumonia (see below).
- For moderate to severe pneumonia due to P. aeruginosa give 50 mg per kg per dose, every 8 hours.
- 50 mg per kg per dose, every 8 hours for febrile neutropenic patients.

Cefepime Injection in Galaxy Container should be used only in pediatric patients who require the entire 1 or 2 g dose and not any fraction thereof.

2.3 Dosage Adjustments in Patients with Renal Impairment

Adult Patients

Adjust the dose of Cefepime Injection in patients with creatinine clearance less than or equal to 60 mL/min to compensate for the slower rate of renal elimination. In these patients, the recommended initial dose of Cefepime Injection should be the same as in patients with CrCL greater than 60 mL/min except in patients undergoing hemodialysis. The recommended doses of Cefepime Injection in patients with renal impairment are presented in Table 2.

When only serum creatinine is available, the following formula (Cockcroft and Gault equation)^1 may be used to estimate creatinine clearance. The serum creatinine should represent a steady state of renal function:

Males: Creatinine Clearance (mL/min) = |  | Weight (kg) x (140 – age)
 |  | 72 x serum creatinine (mg/dL)
Females: 0.85 x above value

Table 2: Recommended Dosing Schedule for Cefepime Injection in Adult Patients With Creatinine Clearance Less Than or Equal to 60 mL/min
Creatinine Clearance (mL/min) | Recommended Maintenance Schedule
Greater than 60 | 500 mg every 12 hours | 1 g every 12 hours | 2 g every 12 hours | 2 g every 8 hours
30–60 | 500 mg every 24 hours | 1 g every 24 hours | 2 g every 24 hours | 2 g every 12 hours
11–29 | 500 mg every 24 hours | 500 mg every 24 hours | 1 g every 24 hours | 2 g every 24 hours
Less than 11 | 250 mg every 24 hours | 250 mg every 24 hours | 500 mg every 24 hours | 1 g every 24 hours
Continuous Ambulatory Peritoneal Dialysis CAPD | 500 mg every 48 hours | 1 g every 48 hours | 2 g every 48 hours | 2 g every 48 hours
Hemodialysis [On hemodialysis days, Cefepime Injection should be administered following hemodialysis. Whenever possible, Cefepime Injection should be administered at the same time each day.] | 1 g on day 1, then 500 mg every 24 hours thereafter |  |  | 1 g every 24 hours

In patients undergoing Continuous Ambulatory Peritoneal Dialysis (CAPD), Cefepime Injection may be administered at the recommended doses at a dosage interval of every 48 hours (see Table 2).

In patients undergoing hemodialysis, approximately 68% of the total amount of cefepime present in the body at the start of dialysis will be removed during a 3-hour dialysis period. The dosage of Cefepime Injection for hemodialysis patients is 1 g on Day 1 followed by 500 mg every 24 hours for the treatment of all infections except febrile neutropenia, which is 1 g every 24 hours.

Cefepime Injection should be administered at the same time each day and following the completion of hemodialysis on hemodialysis days (see Table 2).

Pediatric Patients

Data in pediatric patients with impaired renal function are not available; however, since cefepime pharmacokinetics are similar in adults and pediatric patients [see Clinical Pharmacology (12.3)], changes in the dosing regimen proportional to those in adults (see Table 1 and Table 2) are recommended for pediatric patients.

2.4 Directions for Use of Cefepime Injection in Galaxy Container

Cefepime Injection in Galaxy Container is for intravenous administration using sterile equipment after thawing to room temperature.

Thawing of Plastic Container

Thaw frozen container at room temperature 25°C (77°F) or under refrigeration 5°C (41°F). Do not force thaw by immersion in water baths or by microwave irradiation.[See How Supplied/Storage and Handling (16).]

Check for minute leaks by squeezing container firmly. If leaks are detected, discard solution as sterility may be impaired.

Do not add supplementary medication.

Parenteral drug products should be inspected visually for particulate matter and discoloration prior to administration, whenever solution and container permit.

Visually inspect the container. If the outlet port protector is damaged, detached, or not present, discard container as solution path sterility may be impaired. Components of the solution may precipitate in the frozen state and will dissolve upon reaching room temperature with little or no agitation. Potency is not affected. Agitate after solution has reached room temperature. If after visual inspection the solution remains cloudy or if an insoluble precipitate is noted or if any seals are not intact, the container should be discarded.

Caution: Do not use plastic containers in series connections. Such use could result in air embolism due to residual air being drawn from the primary container before administration of the fluid from the secondary container is complete.

Preparation for intravenous administration.

1. Suspend container from eyelet support.
2. Remove protector from outlet port at bottom of container.
3. Attach administration set. Refer to complete directions accompanying set.

Cefepime Injection should be administered intravenously over approximately 30 minutes.

Intermittent intravenous infusion with a Y-type administration set can be accomplished with compatible solutions. However, during infusion of Cefepime Injection, it is desirable to discontinue the other solution.

Solutions of cefepime, like those of most beta-lactam antibacterial drugs, should not be added to solutions of ampicillin at a concentration greater than 40 mg per mL, and should not be added to metronidazole, vancomycin, gentamicin, tobramycin, netilmicin sulfate or aminophylline because of potential interaction. However, if concurrent therapy with cefepime is indicated, each of these antibacterials can be administered separately.

As with other cephalosporins, the color of Cefepime Injection tend to darken depending on storage conditions; however, when stored as recommended, the product potency is not adversely affected.

3 DOSAGE FORMS AND STRENGTHS

Cefepime Injection is available in the following strengths:

- 1 g in 50 mL (contains 1 g of cefepime as Cefepime Hydrochloride, USP) single-dose Galaxy Container
- 2 g in 100 mL (contains 2 g of cefepime as Cefepime Hydrochloride, USP) single-dose Galaxy Container

4 CONTRAINDICATIONS

Cefepime Injection is contraindicated in patients who have shown immediate hypersensitivity reactions to cefepime or the cephalosporin class of antibacterials, penicillins or other beta-lactam antibacterial drugs.

Solutions containing dextrose may be contraindicated in patients with known allergy to corn or corn products.

5 WARNINGS AND PRECAUTIONS

5.1 Hypersensitivity Reactions

Before therapy with Cefepime Injection is instituted, careful inquiry should be made to determine whether the patient has had previous immediate hypersensitivity reactions to cefepime, cephalosporins, penicillins, or other beta-lactams. Exercise caution if this product is to be given to penicillin-sensitive patients because cross-hypersensitivity among beta-lactam antibacterial drugs has been clearly documented and may occur in up to 10% of patients with a history of penicillin allergy. If an allergic reaction to Cefepime Injection occurs, discontinue the drug and institute appropriate supportive measures. Hypersensitivity reactions can progress to Kounis syndrome, a serious allergic reaction that can result in myocardial infarction.

5.2 Neurotoxicity

Serious adverse reactions have been reported including life-threatening or fatal occurrences of the following: encephalopathy (disturbance of consciousness including confusion, hallucinations, stupor, and coma), aphasia, myoclonus, seizures, and nonconvulsive status epilepticus [see Adverse Reactions (6.2)]. Most cases occurred in patients with renal impairment who did not receive appropriate dosage adjustment. However, some cases of neurotoxicity occurred in patients receiving a dosage adjustment appropriate for their degree of renal impairment.

In the majority of cases, symptoms of neurotoxicity were reversible and resolved after discontinuation of cefepime and/or after hemodialysis. If neurotoxicity associated with cefepime therapy occurs, discontinue cefepime and institute appropriate supportive measures.

5.3 Clostridioides difficile Associated Diarrhea

Clostridioides difficile associated diarrhea (CDAD) has been reported with use of nearly all antibacterial agents, including Cefepime Injection, and may range in severity from mild diarrhea to fatal colitis. Treatment with antibacterial agents alters the normal flora of the colon leading to overgrowth of C. difficile.

C. difficile produces toxins A and B which contribute to the development of CDAD. Hypertoxin-producing strains of C. difficile cause increased morbidity and mortality, as these infections can be refractory to antimicrobial therapy and may require colectomy. CDAD must be considered in all patients who present with diarrhea following antibacterial drug use. Careful medical history is necessary since CDAD has been reported to occur over two months after the administration of antibacterial agents.

If CDAD is suspected or confirmed, ongoing antibacterial drug use not directed against C. difficile may need to be discontinued. Appropriate fluid and electrolyte management, protein supplementation, antibacterial treatment of C. difficile, and surgical evaluation should be instituted as clinically indicated.

5.4 Development of Drug-Resistant Bacteria

Prescribing cefepime in the absence of a proven or strongly suspected bacterial infection is unlikely to provide benefit to the patient and increases the risk of the development of drug-resistant bacteria.

As with other antimicrobials, prolonged use of cefepime may result in overgrowth of nonsusceptible microorganisms. Repeated evaluation of the patient’s condition is essential. Should superinfection occur during therapy, appropriate measures should be taken.

5.5 Drug/Laboratory Test Interactions

Urinary Glucose

The administration of cefepime may result in a false-positive reaction for glucose in the urine when using some methods (e.g. Clinitest tablets) [see Drug Interactions (7.1)].

Coombs' Tests

Positive direct Coombs’ tests have been reported during treatment with cefepime. In patients who develop hemolytic anemia, discontinue the drug and institute appropriate therapy. Positive Coombs’ test may be observed in newborns whose mothers have received cephalosporin antibacterials before parturition.

Prothrombin Time

Many cephalosporins, including cefepime, have been associated with a fall in prothrombin activity. Those at risk include patients with renal or hepatic impairment, or poor nutritional state, as well as patients receiving a protracted course of antibacterial therapy. Prothrombin time should be monitored in patients at risk, and exogenous vitamin K administered as indicated.

6 ADVERSE REACTIONS

The following adverse reactions are discussed in other sections of the labeling:

- Hypersensitivity reactions [see Warnings and Precautions (5.1)]
- Neurotoxicity [see Warnings and Precautions (5.2)]
- Clostridioides difficile-associated diarrhea [see Warnings and Precautions (5.3)]

6.1 Clinical Trials Experience

Because clinical trials are conducted under widely varying conditions, adverse reaction rates observed in the clinical trials of a drug cannot be directly compared to rates in the clinical trials of another drug and may not reflect the rates observed in practice.

In clinical trials using multiple doses of cefepime, 4137 patients were treated with the recommended dosages of cefepime (500 mg to 2 g intravenously every 12 hours). There were no deaths or permanent disabilities thought related to drug toxicity. Sixty‑four (1.5%) patients discontinued medication due to adverse reactions. Thirty-three (51%) of these 64 patients who discontinued therapy did so because of rash. The percentage of cefepime-treated patients who discontinued study drug because of drug-related adverse reactions was similar at daily doses of 500 mg, 1 g, and 2 g every 12 hours (0.8%, 1.1%, and 2%, respectively). However, the incidence of discontinuation due to rash increased with the higher recommended doses.

The following adverse reactions (Table 3) were identified in clinical trials conducted in North America (n=3125 cefepime-treated patients).

Table 3: Adverse Reactions in Cefepime Multiple-Dose Dosing Regimens Clinical Trials in North America
INCIDENCE EQUAL TO OR GREATER THAN 1% | Local adverse reactions (3%), including phlebitis (1.3%), pain and/or inflammation (0.6%) [Local reactions, irrespective of relationship to cefepime in those patients who received intravenous infusion (n=3048).] ; rash (1.1%)
INCIDENCE LESS THAN 1% BUT GREATER THAN 0.1% | Colitis (including pseudomembranous colitis), diarrhea, erythema, fever, headache, nausea, oral moniliasis, pruritus, urticaria, vaginitis, vomiting, anemia

At the higher dose of 2 g every 8 hours, the incidence of adverse reactions was higher among the 795 patients who received this dose of cefepime. They consisted of rash (4%), diarrhea (3%), nausea (2%), vomiting (1%), pruritus (1%), fever (1%), and headache (1%).

The following (Table 4) adverse laboratory changes with cefepime, were seen during clinical trials conducted in North America.

Table 4: Adverse Laboratory Changes in Cefepime Multiple-Dose Dosing Regimens Clinical Trials in North America
INCIDENCE EQUAL TO OR GREATER THAN 1% | Positive Coombs’ test (without hemolysis) (16.2%); decreased phosphorus (2.8%); increased Alanine Transaminase (ALT) (2.8%), Aspartate Transaminase (AST) (2.4%), eosinophils (1.7%); abnormal PTT (1.6%), Prothrombin Time (PT) (1.4%)
INCIDENCE LESS THAN 1% BUT GREATER THAN 0.1% | Increased alkaline phosphatase, Blood Urea Nitrogen (BUN), calcium, creatinine, phosphorus, potassium, total bilirubin; decreased calcium [Hypocalcemia was more common among elderly patients. Clinical consequences from changes in either calcium or phosphorus were not reported.] , hematocrit, neutrophils, platelets, White Blood Cells (WBC)

A similar safety profile was seen in clinical trials of pediatric patients.

6.2 Postmarketing Experience

The following adverse reactions have been identified during post-approval use of Cefepime Injection. Because these reactions are reported voluntarily from a population of uncertain size, it is not always possible to reliably estimate their frequency or establish a causal relationship to drug exposure.

In addition to the adverse reactions reported during North American clinical trials with cefepime, the following adverse reactions have been reported during worldwide postmarketing experience.

Encephalopathy (disturbance of consciousness including confusion, hallucinations, stupor, and coma), aphasia, myoclonus, seizures, and nonconvulsive status epilepticus have been reported [see Warnings and Precautions (5.2)].

Anaphylaxis including anaphylactic shock, transient leukopenia, neutropenia, agranulocytosis, and thrombocytopenia, have been reported.

6.3 Cephalosporin-Class Adverse Reactions

In addition to the adverse reactions listed above that have been observed in patients treated with cefepime, the following adverse reactions and altered laboratory tests have been reported for cephalosporin-class antibacterial drugs:

Kounis syndrome, Stevens-Johnson syndrome, erythema multiforme, toxic epidermal necrolysis, renal dysfunction, toxic nephropathy, aplastic anemia, hemolytic anemia, hemorrhage, fall in prothrombin activity, hepatic dysfunction including cholestasis, and pancytopenia.

7 DRUG INTERACTIONS

7.1 Drug/Laboratory Test Interactions

The administration of cefepime may result in a false-positive reaction for glucose in the urine with certain methods. It is recommended that glucose tests based on enzymatic glucose oxidase reactions be used [see Warning and Precautions (5.5)].

7.2 Aminoglycosides

Renal function should be monitored carefully if high doses of aminoglycosides are to be administered with Cefepime Injection because of the increased potential of nephrotoxicity and ototoxicity of aminoglycoside antibacterial drugs.

7.3 Diuretics

Nephrotoxicity has been reported following concomitant administration of other cephalosporins with potent diuretics such as furosemide.

8 USE IN SPECIFIC POPULATIONS

8.1 Pregnancy

Risk summary

There are no cases of cefepime exposure during pregnancy reported from postmarketing experience or from clinical trials. Available data from published observational studies and case reports over several decades with cephalosporin use in pregnant women have not established drug-associated risks of major birth defects, miscarriage or adverse maternal or fetal outcomes (see Data).

Cefepime was not associated with adverse developmental outcomes in rats, mice, or rabbits when administered parenterally during the period of organogenesis. The doses used in these studies were 1.6 times (rats), approximately equal to (mice) and 0.3 times (rabbits) the maximum recommended clinical dose (see Data).

The estimated background risk of major birth defects and miscarriage for the indicated population is unknown. All pregnancies have a background risk of birth defect, loss, or other adverse outcomes. In the U.S. general population, the estimated background risk of major birth defects and miscarriage in clinically recognized pregnancies is 2-4% and 15-20%, respectively.

Data

Human Data

While available studies cannot definitively establish the absence of risk, published data from case-control studies and case reports over several decades have not identified an association with cephalosporin use during pregnancy and major birth defects, miscarriage, or other adverse maternal or fetal outcomes. Available studies have methodologic limitations, including small sample size, retrospective data collection, and inconsistent comparator groups.

Animal data

Cefepime was not embryocidal and did not cause fetal malformations when administered parenterally during the period of organogenesis to rats at doses up to 1000 mg/kg/day, to mice at doses up to 1200 mg/kg/day, or to rabbits at doses up to 100 mg/kg/day. These doses are 1.6 times (rats), approximately equal to (mice), and 0.3 times (rabbits) the maximum recommended clinical dose based on body surface area.

8.2 Lactation

Risk Summary

Cefepime is present in human milk at low concentration (0.5 mcg/mL). A nursing infant consuming approximately 1000 mL of human milk per day would receive approximately 0.5 mg of cefepime per day. There is no information regarding effects of cefepime on milk production or on the breastfed infant. The developmental and health benefits of breastfeeding should be considered along with the mother’s clinical need for cefepime and any potential adverse effects on the breastfed child from cefepime or from the underlying maternal condition.

8.4 Pediatric Use

The safety and effectiveness of cefepime in the treatment of uncomplicated and complicated urinary tract infections (including pyelonephritis), uncomplicated skin and skin structure infections, pneumonia, and as empiric therapy for febrile neutropenic patients have been established in the age groups 2 months up to 16 years. Use of Cefepime Injection in these age groups is supported by evidence from adequate and well-controlled studies of cefepime in adults with additional pharmacokinetic and safety data from pediatric trials [see Clinical Pharmacology (12)].

Safety and effectiveness in pediatric patients below the age of 2 months have not been established. There are insufficient clinical data to support the use of Cefepime Injection in pediatric patients under 2 months of age or for the treatment of serious infections in the pediatric population where the suspected or proven pathogen is Haemophilus influenzae type b. In those patients in whom meningeal seeding from a distant infection site or in whom meningitis is suspected or documented, an alternate agent with demonstrated clinical efficacy in this setting should be used.

Cefepime Injection in Galaxy Container should be used only in pediatric patients who require the entire 1 or 2 g dose and not any fraction thereof.

8.5 Geriatric Use

Of the more than 6400 adults treated with cefepime in clinical studies, 35% were 65 years or older while 16% were 75 years or older. When geriatric patients received the usual recommended adult dose, clinical efficacy and safety were comparable to clinical efficacy and safety in nongeriatric adult patients.

Serious adverse events have occurred in geriatric patients with renal impairment given unadjusted doses of cefepime, including life-threatening or fatal occurrences of the following: encephalopathy, myoclonus, and seizures [see Warnings and Precautions (5) and Adverse Reactions (6)].

This drug is known to be substantially excreted by the kidney, and the risk of toxic reactions to this drug may be greater in patients with impaired renal function. Because elderly patients are more likely to have decreased renal function, care should be taken in dose selection, and renal function should be monitored [see Clinical Pharmacology (12), Warnings and Precautions (5), and Dosage and Administration (2)].

8.6 Renal Impairment

Adjust the dose of Cefepime Injection in patients with creatinine clearance less than or equal to 60 mL/min to compensate for the slower rate of renal elimination [see Dosage and Administration (2.3)].

10 OVERDOSAGE

Patients who receive an overdose should be carefully observed and given supportive treatment. In the presence of renal impairment, hemodialysis, not peritoneal dialysis, is recommended to aid in the removal of cefepime from the body. Accidental overdosing has occurred when large doses were given to patients with impaired renal function. Symptoms of overdose include encephalopathy (disturbance of consciousness including confusion, hallucinations, stupor, and coma), myoclonus, seizures, and neuromuscular excitability [see Warnings and Precautions (5), Adverse Reactions (6), and Dosage and Administration (2)].

11 DESCRIPTION

Cefepime Injection in Galaxy Container is a sterile, injectable product consisting of Cefepime Hydrochloride, USP, a semi-synthetic, broad spectrum, cephalosporin antibacterial for parenteral administration. The chemical name is 1-[[(6R,7R)-7-[2-(2-Amino-4-thiazolyl) glyoxylamido]-2-carboxy-8-oxo-5-thia-1-azabicyclo[4.2.0] oct-2-en-3-yl]methyl]-1-methylpyrrolidinium chloride, 7^2-(Z)-(O-methyloxime), monohydrochloride, monohydrate, which corresponds to the following structural formula:

Cefepime hydrochloride (monohydrate) has a molecular mass of 571.50 and a molecular formula of C19H25ClN6O5S2•HCl•H2O.

Cefepime Injection in Galaxy Container is a frozen, iso-osmotic, sterile, non-pyrogenic premixed solution supplied for intravenous administration in strengths equivalent to 1 g and 2 g of cefepime [see Dosage and Administration (2)]. It contains the equivalent of not less than 90 percent and not more than 115 percent of the labeled amount of cefepime (C19H24N6O5S2).

The solution is intended for intravenous use after thawing to room temperature. The components and dosage formulations are given in the table below:

Table 5: Cefepime Injection in Galaxy Containers Premixed Frozen Solution
Component [Cefepime is present in the formulation as Cefepime Hydrochloride, USP. The amounts of Dextrose Hydrous, USP and L-Arginine, USP are approximate.] | Function | Dosage Formulations
Component [Cefepime is present in the formulation as Cefepime Hydrochloride, USP. The amounts of Dextrose Hydrous, USP and L-Arginine, USP are approximate.] | Function | 1 g in 50 mL | 2 g in 100 mL
Cefepime | active ingredient | 1 g | 2 g
Dextrose Hydrous, USP | osmolality adjuster | 1.03 g | 2.06 g
L-Arginine, USP [The pH may have been adjusted with hydrochloric acid and/or additional L-Arginine, USP. The pH is 4.0 – 6.0.] | pH adjuster | 725 mg | 1.45 g
Hydrochloric Acid | pH adjuster | As needed | As needed
Water for Injection, USP | vehicle | q.s. [This is an abbreviation for sufficient quantity.] 50 mL | q.s. 100 mL

Cefepime Injection will range in color from colorless to amber.

The plastic container is fabricated from a specially designed multilayer plastic. Solutions are in contact with the polyethylene layer of this container and can leach out certain chemical components of the plastic in very small amounts within the expiration period. The suitability of the plastic has been confirmed in tests in animals according to the USP biological tests for plastic containers, as well as by tissue culture toxicity studies.

12 CLINICAL PHARMACOLOGY

12.1 Mechanism of Action

Cefepime is an antibacterial drug. [See Microbiology (12.4)]

12.2 Pharmacodynamics

Similar to other beta-lactam antibacterial drugs, the time that the unbound plasma concentration of cefepime exceeds the MIC of the infecting organism has been shown to best correlate with efficacy in animal models of infection. However, the pharmacokinetic/pharmacodynamic relationship for cefepime has not been evaluated in patients.

12.3 Pharmacokinetics

Pharmacokinetic parameters for cefepime in healthy adult male volunteers (n=9) following single 30-minute intravenous infusions of cefepime 500 mg, 1 g, and 2 g are summarized in Table 6. Elimination of cefepime is principally via renal excretion with an average (±SD) half-life of 2 (±0.3) hours and total body clearance of 120 (±8) mL/min in healthy volunteers. Cefepime pharmacokinetics are linear over the range 250 mg to 2 g. There is no evidence of accumulation in healthy adult male volunteers (n=7) receiving clinically relevant doses for a period of 9 days.

Table 6: Mean Pharmacokinetic Parameters for Cefepime (±SD), Intravenous Administration
 | CEFEPIME
Parameter | 500 mg IV | 1 g IV | 2 g IV
Cmax, mcg/mL | 39.1 (3.5) | 81.7 (5.1) | 163.9 (25.3)
AUC, h•mcg/mL | 70.8 (6.7) | 148.5 (15.1) | 284.8 (30.6)
Number of subjects (male) | 9 | 9 | 9

Distribution

The average steady-state volume of distribution of cefepime is 18.0 (±2.0) L. The serum protein binding of cefepime is approximately 20% and is independent of its concentration in serum.

Concentrations of cefepime achieved in specific tissues and body fluids are listed in Table 7.

Table 7: Mean Concentrations of Cefepime in Specific Body Fluids (mcg/mL) or Tissues (mcg/g)
Tissue or Fluid | Dose/Route | # of Patients | Mean Time of Sample Post-Dose (h) | Mean Concentration
Blister Fluid | 2 g IV | 6 | 1.5 | 81.4 mcg/mL
Bronchial Mucosa | 2 g IV | 20 | 4.8 | 24.1 mcg/g
Sputum | 2 g IV | 5 | 4 | 7.4 mcg/mL
Urine | 500 mg IV | 8 | 0-4 | 292 mcg/mL
 | 1 g IV | 12 | 0-4 | 926 mcg/mL
 | 2 g IV | 12 | 0-4 | 3120 mcg/mL
Bile | 2 g IV | 26 | 9.4 | 17.8 mcg/mL
Peritoneal Fluid | 2 g IV | 19 | 4.4 | 18.3 mcg/mL
Appendix | 2 g IV | 31 | 5.7 | 5.2 mcg/g
Gall Bladder | 2 g IV | 38 | 8.9 | 11.9 mcg/g
Prostate | 2 g IV | 5 | 1 | 31.5 mcg/g

Data suggest that cefepime does cross the inflamed blood-brain barrier. The clinical relevance of these data is uncertain at this time.

Metabolism and Excretion

Cefepime is metabolized to N-methylpyrrolidine (NMP), which is rapidly converted to the N-oxide (NMP-N-oxide). Urinary recovery of unchanged cefepime accounts for approximately 85% of the administered dose. Less than 1% of the administered dose is recovered from urine as NMP, 6.8% as NMP-N-oxide, and 2.5% as an epimer of cefepime. Because renal excretion is a significant pathway of elimination, patients with renal dysfunction and patients undergoing hemodialysis require dosage adjustment [see Dosage and Administration (2)].

Specific Populations

Patients with Renal Impairment

Cefepime pharmacokinetics have been investigated in patients with various degrees of renal impairment (n=30). The average half-life in patients requiring hemodialysis was 13.5 (±2.7) hours and in patients requiring continuous peritoneal dialysis was 19 (±2.0) hours. Cefepime total body clearance decreased proportionally with creatinine clearance in patients with abnormal renal function, which serves as the basis for dosage adjustment recommendations in this group of patients [see Dosage and Administration (2)].

Patients with Hepatic Impairment

The pharmacokinetics of cefepime were unaltered in patients with hepatic impairment who received a single 1 g dose (n=11).

Geriatric Patients

Cefepime pharmacokinetics have been investigated in elderly (65 years of age and older) men (n=12) and women (n=12) whose mean (SD) creatinine clearance was 74.0 (±15.0) mL/min. There appeared to be a decrease in cefepime total body clearance as a function of creatinine clearance. Therefore, dosage administration of cefepime in the elderly should be adjusted as appropriate if the patient’s creatinine clearance is 60 mL/min or less [see Dosage and Administration (2)].

Pediatric Patients

Cefepime pharmacokinetics have been evaluated in pediatric patients from 2 months to 11 years of age following single and multiple doses on every 8 hours (n=29) and every 12 hours (n=13) schedules. Following a single intravenous dose, total body clearance and the steady-state volume of distribution averaged 3.3 (±1.0) mL/min/kg and 0.3 (±0.1) L/kg, respectively. The urinary recovery of unchanged cefepime was 60.4 (±30.4)% of the administered dose, and the average renal clearance was 2.0 (±1.1) mL/min/kg. There were no significant effects of age or gender (25 male vs. 17 female) on total body clearance or volume of distribution, corrected for body weight. No accumulation was seen when cefepime was given at 50 mg per kg every 12 hours (n=13), while Cmax, AUC, and t1/2 were increased about 15% at steady state after 50 mg per kg every 8 hours. The exposure to cefepime following a 50 mg per kg intravenous dose in a pediatric patient is comparable to that in an adult treated with a 2 g intravenous dose.

12.4 Microbiology

Mechanism of Action

Cefepime is a bactericidal agent that acts by inhibition of bacterial cell wall synthesis. Cefepime has a broad spectrum of in vitro activity that encompasses a wide range of Gram-positive and Gram-negative bacteria. Cefepime has a low affinity for chromosomally-encoded beta-lactamases. Cefepime is highly resistant to hydrolysis by most beta-lactamases and exhibits rapid penetration into Gram-negative bacterial cells. Within bacterial cells, the molecular targets of cefepime are the penicillin binding proteins (PBP).

Antimicrobial Activity

Cefepime has been shown to be active against most isolates of the following bacteria, both in vitro and in clinical infections [see Indications and Usage (1)]:

Gram-negative bacteria

Enterobacter spp.
Escherichia coli
Klebsiella pneumoniae
Proteus mirabilis
Pseudomonas aeruginosa

Gram-positive bacteria

Staphylococcus aureus (methicillin-susceptible isolates only)
Streptococcus pneumoniae
Streptococcus pyogenes (Lancefield’s Group A streptococci)
Viridans group streptococci

The following in vitro data are available, but their clinical significance is unknown. At least 90 percent of the following bacteria exhibit an in vitro minimum inhibitory concentration (MIC) less than or equal to the susceptible breakpoint for cefepime against isolates of similar genus or organism group. However, the efficacy of cefepime in treating clinical infections due to these bacteria has not been established in adequate and well-controlled clinical trials.

Gram-positive bacteria

Staphylococcus epidermidis (methicillin-susceptible isolates only)
Staphylococcus saprophyticus
Streptococcus agalactiae (Lancefield’s Group B streptococci)

NOTE: Most isolates of enterococci, eg, Enterococcus faecalis, and methicillin-resistant staphylococci are resistant to cefepime.

Gram-negative bacteria

Acinetobacter calcoaceticus subsp. lwoffii
Citrobacter diversus
Citrobacter freundii
Enterobacter agglomerans
Haemophilus influenzae
Hafnia alvei
Klebsiella oxytoca
Moraxella catarrhalis
Morganella morganii
Proteus vulgaris
Providencia rettgeri
Providencia stuartii
Serratia marcescens

NOTE: Cefepime is inactive against many isolates of Stenotrophomonas (formerly Xanthomonas maltophilia and Pseudomonas maltophilia).

Susceptibility Test Methods

For specific information regarding susceptibility test interpretive criteria and associated test methods and quality control standards recognized by FDA for this drug, please see: http://www.fda.gov/STIC.

13 NONCLINICAL TOXICOLOGY

13.1 Carcinogenesis, Mutagenesis, Impairment of Fertility

No animal carcinogenicity studies have been conducted with cefepime. In chromosomal aberration studies, cefepime was positive for clastogenicity in primary human lymphocytes, but negative in Chinese hamster ovary cells. In other in vitro assays (bacterial and mammalian cell mutation, DNA repair in primary rat hepatocytes, and sister chromatid exchange in human lymphocytes), cefepime was negative for genotoxic effects. Moreover, in vivo assessments of cefepime in mice (2 chromosomal aberration and 2 micronucleus studies) were negative for clastogenicity. No untoward effects on fertility were observed in rats when cefepime was administered subcutaneously at doses up to 1000 mg/kg/day (1.6 times the recommended maximum human dose based on body surface area).

14 CLINICAL STUDIES

14.1 Febrile Neutropenic Patients

The safety and efficacy of empiric cefepime monotherapy of febrile neutropenic patients have been assessed in two multicenter, randomized trials, comparing cefepime monotherapy (at a dose of 2 g intravenously every 8 hours) to ceftazidime monotherapy (at a dose of 2 g intravenously every 8 hours). These studies comprised 317 evaluable patients. Table 8 describes the characteristics of the evaluable patient population.

Table 8: Demographics of Evaluable Patients (First Episodes Only)
 | Cefepime | Ceftazidime
Total | 164 | 153
Median age (yr) | 56 (range, 18-82) | 55 (range, 16-84)
Male | 86 (52%) | 85 (56%)
Female | 78 (48%) | 68 (44%)
Leukemia | 65 (40%) | 52 (34%)
Other hematologic malignancies | 43 (26%) | 36 (24%)
Solid tumor | 54 (33%) | 56 (37%)
Median ANC nadir (cells per microliter) | 20 (range, 0-500) | 20 (range, 0-500)
Median duration of neutropenia (days) | 6 (range, 0-39) | 6 (range, 0-32)
Indwelling venous catheter | 97 (59%) | 86 (56%)
Prophylactic antibiotics | 62 (38%) | 64 (42%)
Bone marrow graft | 9 (5%) | 7 (5%)
SBP less than 90 mm Hg at entry | 7 (4%) | 2 (1%)
ANC = absolute neutrophil count; SBP = systolic blood pressure

Table 9 describes the clinical response rates observed. For all outcome measures, cefepime was therapeutically equivalent to ceftazidime.

Table 9: Pooled Response Rates for Empiric Therapy of Febrile Neutropenic Patients
 | % Response
 | Cefepime | Ceftazidime
Outcome Measures | (n = 164) | (n = 153)
Primary episode resolved with no treatment modification, no new febrile episodes or infection, and oral antibiotics allowed for completion of treatment | 51 | 55
Primary episode resolved with no treatment modification, no new febrile episodes or infection, and no post-treatment oral antibiotics | 34 | 39
Survival, any treatment modification allowed | 93 | 97
Primary episode resolved with no treatment modification and oral antibiotics allowed for completion of treatment | 62 | 67
Primary episode resolved with no treatment modification and no post-treatment oral antibiotics | 46 | 51

Insufficient data exist to support the efficacy of cefepime monotherapy in patients at high risk for severe infection (including patients with a history of recent bone marrow transplantation, with hypotension at presentation, with an underlying hematologic malignancy, or with severe or prolonged neutropenia). No data are available in patients with septic shock.

14.2 Complicated Intra-abdominal Infections

Patients hospitalized with complicated intra-abdominal infections participated in a randomized, double-blind, multicenter trial comparing the combination of cefepime (2 g every 12 hours) plus intravenous metronidazole (500 mg every 6 hours) versus imipenem/cilastatin (500 mg every 6 hours) for a maximum duration of 14 days of therapy. The study was designed to demonstrate equivalence of the two therapies. The primary analyses were conducted on the protocol-valid population, which consisted of those with a surgically confirmed complicated infection, at least one pathogen isolated pretreatment, at least 5 days of treatment, and a 4 to 6 week follow-up assessment for cured patients. Subjects in the imipenem/cilastatin arm had higher APACHE II scores at baseline. The treatment groups were otherwise generally comparable with regard to their pretreatment characteristics. The overall clinical cure rate among the protocol-valid patients was 81% (51 cured/63 evaluable patients) in the cefepime plus metronidazole group and 66% (62/94) in the imipenem/cilastatin group. The observed differences in efficacy may have been due to a greater proportion of patients with high APACHE II scores in the imipenem/cilastatin group.

15 REFERENCES

1. Cockcroft DW, Gault MH. Prediction of creatinine clearance from serum creatinine. Nephron. 1976; 16:31-41.

16 HOW SUPPLIED/STORAGE AND HANDLING

Cefepime Injection is supplied as a frozen, iso-osmotic, sterile, nonpyrogenic solution in 50 mL and 100 mL single-dose Galaxy Containers as follows:

1 g [Based on cefepime activity] in 50 mL | Supplied 24/box | NDC 0338-1301-41
2 g in 100 mL | Supplied 12/box | NDC 0338-1301-48

Store at or below –20°C (-4°F).

Handle frozen product containers with care. Product containers may be fragile in the frozen state.

Thaw frozen container at room temperature 25°C (77°F) or under refrigeration 5°C (41°F). Do not force thaw by immersion in water baths or by microwave irradiation.

The thawed solution remains stable for 7 days under refrigeration 5°C (41°F) or 24 hours at room temperature 25°C (77°F). Do not refreeze. [See Dosage and Administration (2.4)].

17 PATIENT COUNSELING INFORMATION

Antibacterial Resistance
Patients should be counseled that antibacterial drugs including Cefepime Injection should only be used to treat bacterial infections. They do not treat viral infections (e.g., the common cold). When Cefepime Injection is prescribed to treat a bacterial infection, patients should be told that although it is common to feel better early in the course of therapy, the medication should be taken exactly as directed. Skipping doses or not completing the full course of therapy may (1) decrease the effectiveness of the immediate treatment and (2) increase the likelihood that bacteria will develop resistance and will not be treatable by Cefepime Injection or other antibacterial drugs in the future.
Diarrhea
Diarrhea is a common problem caused by antibacterial drugs, which usually ends when the antibiotic is discontinued. Sometimes after starting treatment with antibacterial drugs, patients can develop watery and bloody stools (with or without stomach cramps and fever) even as late as two or more months after having taken the last dose of the antibacterial drug. If this occurs, patients should be instructed to contact their physician as soon as possible.
Neurotoxicity
Advise patients of neurological adverse events that could occur with Cefepime Injection use. Instruct patients or their caregivers to inform their healthcare provider at once of any neurological signs and symptoms, including encephalopathy (disturbance of consciousness including confusion, hallucinations, stupor, and coma), aphasia (disturbance of speaking and understanding spoken and written language), myoclonus, seizures and nonconvulsive status epilepticus, for immediate treatment, dosage adjustment, or discontinuation of Cefepime Injection.

Manufactured by:

Baxter Healthcare Corporation

Deerfield, IL 60015

Baxter and Galaxy are trademarks of Baxter International Inc. or its subsidiaries.

Clinitest is a registered trademark of Siemens Healthcare Diagnostics Inc.

Any other trademarks, product names or brand images appearing herein are the property of their respective owners.

07-19-06-951

PACKAGE LABEL - PRINCIPLE DISPLAY PANEL

Container Label

Baxter 1 g

Cefepime Injection

GALAXY
Single-Dose
Container

50 mL
Iso-osmotic

NDC 0338-1301-41
Code 2G3578

Each 50 mL contains: Cefepime Hydrochloride, USP equivalent to 1 g of

cefepime with approx. 1.03 g of Dextrose Hydrous, USP added to adjust

osmolality. Approx. 725 mg of L-Arginine, USP added per g of cefepime to

adjust the pH. The pH may have been adjusted with hydrochloric acid and/or

additional L-Arginine, USP. The pH is 4.0 - 6.0.

Dosage: Intravenously as directed by a physician. See insert.

Cautions: Do not add supplementary medication. Must not be used in series

connections. Check for minute leaks and solution clarity.

Store at or below -20°C/-4°F. Thaw at room temperature (25°C/77°F) or under

refrigeration (5°C/41°F). DO NOT FORCE THAW BY IMMERSION IN WATER BATHS OR BY MICROWAVE IRRADIATION. Thawed solution remains stable for

7 days under refrigeration (5°C/41°F) or 24 hours at room temperature (25°C/77°F). Do not

refreeze.

Rx Only

Baxter and GALAXY are registered trademarks of Baxter International Inc.

Baxter Healthcare Corporation

Deerfield, IL 60015 USA
PL 2040 Plastic

Made in USA
07-34-63-744

Carton Label_panel 1 of 3

Thaw at room temperature (25°C/77°F) or under refrigeration (5°C/41°F). DO NOT FORCE THAW BY IMMERSION IN WATER BATHS OR BY MICROWAVE IRRADIATION. Thawed solution remains stable for 7 days under refrigeration (5°C/41°F) or 24 hours at room
temperature (25°C/77°F). Do not refreeze.

Handle frozen product containers with care. Product containers may be fragile in the frozen state.

Baxter and Galaxy are registered trademarks of Baxter International Inc.

Baxter Healthcare Corporation, Deerfield, IL 60015 USA

07-04-65-195

Made in USA

PL 2040 Plastic

Baxter Logo

1 g

Cefepime Injection

Rx Only

Carton Label_panel 2 of 3

12 - 50 mL Single-Dose Containers. Iso-osmotic. NDC 0338-1301-41

Store at or below -20°C/-4°F. Do not refreeze. Code 2G3578

*BAR CODE POSITION ONLY
(01) 20303381301419

Carton Label_panel 3 of 3

GALAXY Container
Sterile Nonpyrogenic

Each 50 mL contains: Cefepime Hydrochloride, USP equivalent to 1 g of cefepime with approx. 1.03 g of Dextrose Hydrous, USP added to adjust osmolality. Approx. 725 mg of L-Arginine, USP added per g of cefepime to adjust the pH. The pH may have been adjusted with hydrochloric acid and/or additional L-Arginine, USP. The pH is 4.0 - 6.0.

Dosage: Intravenously as directed by a physician. See insert.

Cautions: Do not add supplementary medication. Must not be used in series connections. Check for minute leaks and solution clarity. Check for minute leaks by squeezing thawed bag firmly. If leaks are found, discard bag as sterility may be impaired. Do not use unless solution is clear.